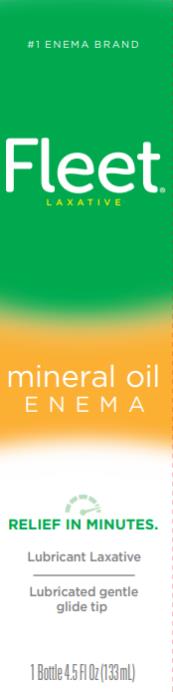 DRUG LABEL: FLEET
NDC: 0132-0301 | Form: ENEMA
Manufacturer: C.B. Fleet Company, Inc.
Category: otc | Type: HUMAN OTC DRUG LABEL
Date: 20231026

ACTIVE INGREDIENTS: MINERAL OIL 100 g/100 mL

Fleet Mineral Oil 0132-0301-40

Drug Facts

Active ingredient (in each 118 mL delivered dose)

Mineral oil 100%

Purpose

Lubricant laxative

Uses

- for relief of fecal impaction
- for relief of occasional constipation
- for removal of residue after barium administration

This product usually produces a bowel movement in 2 to 15 minutes.

Warnings

For rectal use only.

Do not use

when abdominal pain, nausea, or vomiting are present unless directed by a doctor.

Ask a doctor before using this product if you

- have a sudden change in bowel habits lasting more than 2 weeks
- already used a laxative for more than 1 week

Stop use and ask a doctor if you have

- rectal bleeding
- no bowel movement within 15 minutes of using this product

These symptoms may indicate a serious condition.

If pregnant or breast-feeding,

ask a health professional before use.

Keep out of reach of children.

If swallowed, get medical help or contact a Poison Control Center right away.

Directions

Single Daily Dosage (per 24 hours)

adults and children 12 years and over | 1 bottle per day
children 2 to under 12 years | one-half bottle
children under 2 years | DO NOT USE

Other information

- sodium-free

Inactive Ingredients

none

Questions?

1-866-255-6960 or www.fleetlabs.com

PRINCIPAL DISPLAY PANEL

Fleet®
Laxative

Mineral Oil enema
lubricant laxative
1 bottle - 4.5 FL OZ (133 mL)